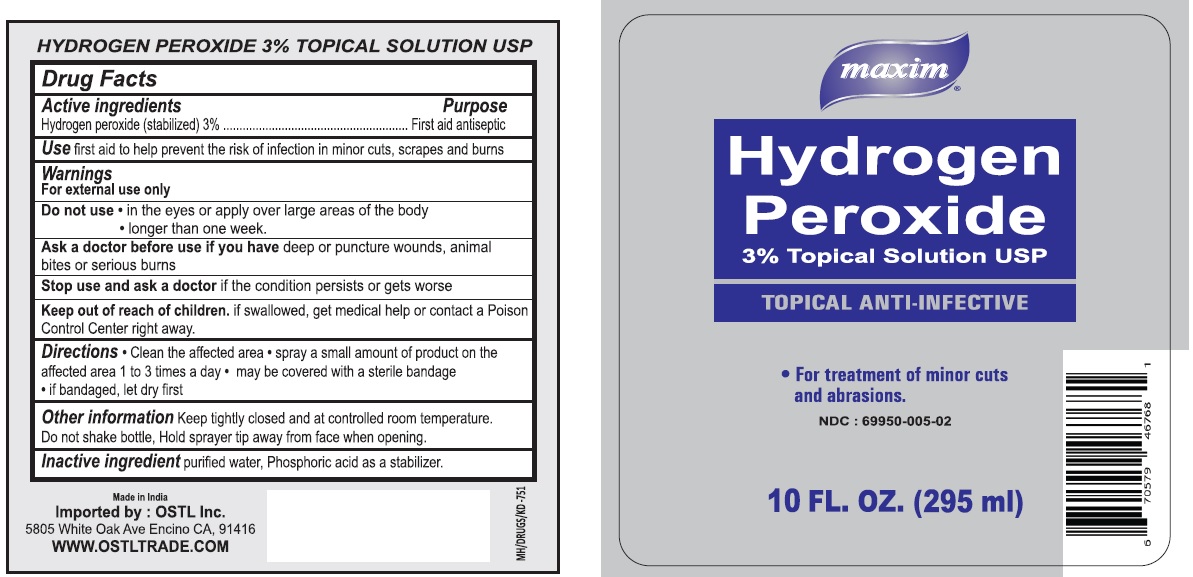 DRUG LABEL: maxim Hydrogen Peroxide
NDC: 69950-005 | Form: LIQUID
Manufacturer: Ostl, Inc.
Category: otc | Type: HUMAN OTC DRUG LABEL
Date: 20160522

ACTIVE INGREDIENTS: HYDROGEN PEROXIDE 30 mg/1 mL
INACTIVE INGREDIENTS: WATER; PHOSPHORIC ACID

maxim SOLUTION OF Hydrogen Peroxide

Active ingredients

Hydrogen peroxide (stabilized) 3%

Purpose

First aid antiseptic

Keep out of reach of children. if swallowed, get medical help or contact a Poison Control Centre right away.

INDICATIONS AND USAGE

Use first aid to help prevent the risk of infection in minor cuts, scrapes and burns

Warnings

For external use only
Do not use • in the eyes or apply over large areas of the body

• longer than one week

Ask a doctor before use if you have deep or puncture wounds, animal bites or serious burns.

Stop use and ask a doctor if the condition persists or gets worse

DOSAGE AND ADMINISTRATION

Directions • Clean the affected area • spray a small amount of product on the affected area 1 to 3 times a day • may be covered with a sterile bandage • if bandaged, let dry first

Inactive ingredient purified water, Phosphoric acid as a stabilizer

Other information Keep tightly closed and at controlled room temperature.

Do not shake bottle, Hold sprayer tip away from face when opening.

Hydrogen Peroxide 3% Topical Solution USP

TOPICAL ANTI-INFECTIVE

For treatment of minor cuts and abrasions.

Made in India

Imported by : OSTL Inc.

5805 White Oak Ave Encino CA, 91416

WWW.OSTLTRADE.COM